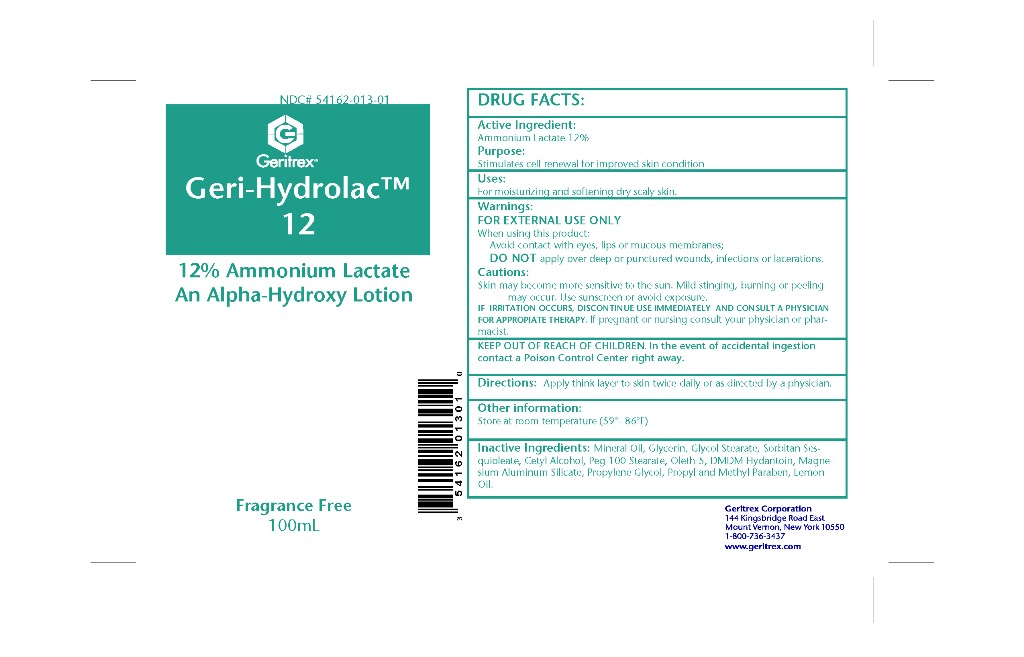 DRUG LABEL: Geri-Hydrolac
NDC: 54162-013 | Form: LOTION
Manufacturer: GERITREX CORP
Category: otc | Type: HUMAN OTC DRUG LABEL
Date: 20130510

ACTIVE INGREDIENTS: AMMONIUM LACTATE 12 g/100 g
INACTIVE INGREDIENTS: WATER; LIGHT MINERAL OIL; GLYCERIN; PEG-100 STEARATE; SORBITAN SESQUIOLEATE; CETYL ALCOHOL; OLETH-5; DMDM HYDANTOIN; MAGNESIUM ALUMINUM SILICATE; PROPYLENE GLYCOL; PROPYLPARABEN; METHYLPARABEN; LEMON OIL

Geri-Hydrolac 12% Lotion

Drug Facts

Active Ingredient Ammonium Lactate 12%

Purpose: Stimulates cell renewal for improved skin conditon

Uses

For moisturizing and softening dry skin

Directions

Apply thin layer to the skin twice daily or as directed by a physician

Warnings

FOR EXTERNAL USE ONLY

When using this product:

Avoid contact with eyes, lips or mucous membranes

DO NOT apply over deep or punctured wounds, infections or lacerations.

Skin may become more sensitive to the sun, mild stinging, burning or peeling

may occur. Use sunscreen or avoid exposure.

If irritation occurs. Discontinue use immediately and consult physician for appropiate therapy. If pregnant or nursing consult

your physician or pharmacist

INACTIVE INGREDIENT

water, Mineral oil, Glycerin, Sorbitan sesquioleate, Cetyl alcohol, Peg-100 stearate, Oleth-5, DMDM Hydantoin,

Magnesium Aluminum silicate, Propylene glycol, propyl and methyl parabens, Lemon oil

Keep out of reach of children

In the event of accidental ingestion contact a Posion Control Center right away

DOSAGE AND ADMINISTRATION

Twice daily or as directed by a physician